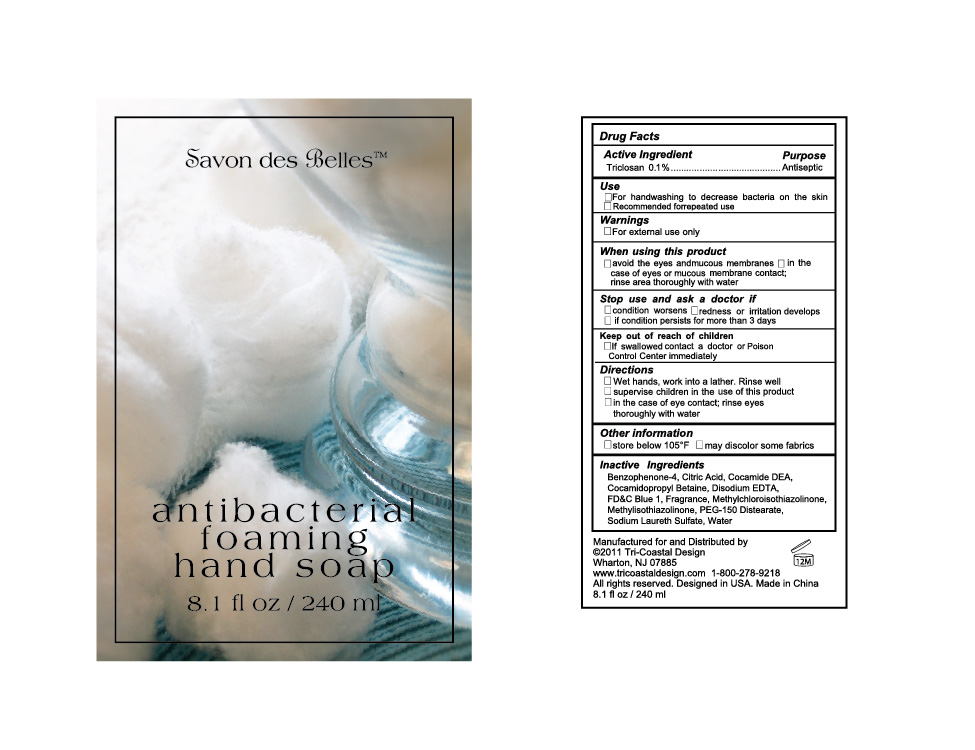 DRUG LABEL: anti-bacterial foaming 
NDC: 49852-011 | Form: SOAP
Manufacturer: Tri-Coastal Design Company Inc. 
Category: otc | Type: HUMAN OTC DRUG LABEL
Date: 20110812

ACTIVE INGREDIENTS: TRICLOSAN 0.1 mL/100 mL
INACTIVE INGREDIENTS: BENZOPHENONE; CITRIC ACID MONOHYDRATE; COCO DIETHANOLAMIDE; COCAMIDOPROPYL BETAINE; EDETATE DISODIUM; FD&C BLUE NO. 1; METHYLCHLOROISOTHIAZOLINONE; METHYLISOTHIAZOLINONE; PEG-150 DISTEARATE; SODIUM LAURETH SULFATE; WATER

Drug Facts

Active Ingredient

Triclosan 0.1%

Purpose

Antiseptic

Uses

- For handwashing to decrease bacteria on the skin
- Recommended for repeated use

Warnings

For external use only

When using this product

- avoid the eyes and mucous membranes
- in the case of eyes or mucous membrane contact; rinse area thoroughly with water

Stop use and ask a doctor if

- condition worsens
- redness or irritation develops
- if condition persists for more than 3 days

Keep out of reach of children

If swallowed contact a doctor or Poison Control Center immediately.

Directions

- Wet hands, work into a lather. Rinse well
- supervise children in the use of this product
- in the case of eye contact, rinse eyes thoroughly with water

Other information

- store below 105F
- may discolor some fabrics

Inactive Ingredients

Benzophenone-4, Citric Acid, Cocamide DEA, Cocamidopropyl Betaine, Disodium EDTA, FDC Blue 1, Fragrance, Methylchloroisothiazolinone, Methylisothiazolinone, PEG-150 Distearate, Sodium Laureth Sulfate, Water

Package Label